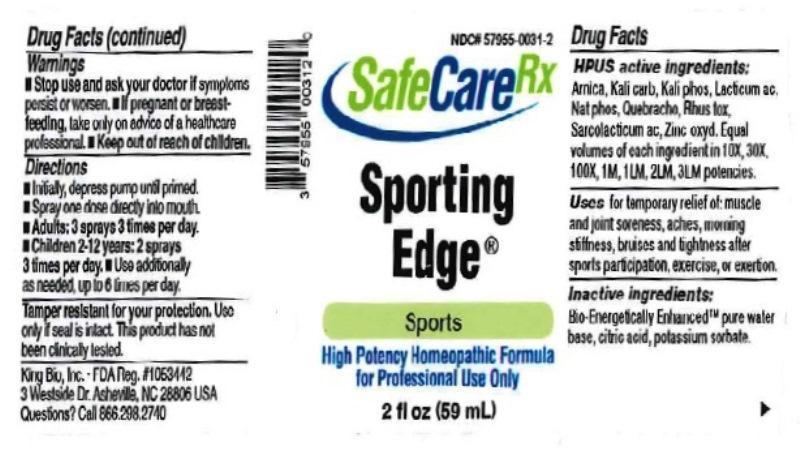 DRUG LABEL: Sporting Edge
NDC: 57955-0031 | Form: LIQUID
Manufacturer: King Bio Inc.
Category: homeopathic | Type: HUMAN OTC DRUG LABEL
Date: 20161104

ACTIVE INGREDIENTS: ARNICA MONTANA 10 [hp_X]/59 mL; POTASSIUM CARBONATE 10 [hp_X]/59 mL; POTASSIUM PHOSPHATE, DIBASIC 10 [hp_X]/59 mL; LACTIC ACID, DL- 10 [hp_X]/59 mL; SODIUM PHOSPHATE, DIBASIC, HEPTAHYDRATE 10 [hp_X]/59 mL; ASPIDOSPERMA QUEBRACHO-BLANCO BARK 10 [hp_X]/59 mL; TOXICODENDRON PUBESCENS LEAF 10 [hp_X]/59 mL; LACTIC ACID, L- 10 [hp_X]/59 mL; ZINC OXIDE 10 [hp_X]/59 mL
INACTIVE INGREDIENTS: WATER; ANHYDROUS CITRIC ACID; POTASSIUM SORBATE

Sporting Edge™

ACTIVE INGREDIENT

Drug Facts__________________________________________________________________________________________________________

HPUS active ingredients: Arnica montana, Kali carbonicum, Kali phosphoricum, Lacticum acidum, Natrum phosphoricum, Quebracho, Rhus toxicodendron, Sarcolacticum acidum, Zincum oxydatum. Equal volumes of each ingredient in 10X, 30X, 100X, 1M, 1LM, 2LM, 3LM potencies.

INDICATIONS AND USAGE

Uses for temporary relief of: muscle and joint soreness, aches, morning stiffness, bruises and tightness after sports participation, exercise, or exertion.

Inactive Ingredients:

Bio-Energetically Enhanced™ pure water, citric acid and potassium sorbate.

Warnings

- Stop use and ask your doctor if symptoms persist or worsen.
- If pregnant or breast-feeding, take only on advice of a healthcare professional.

- Keep out of reach of children.

Directions

- Initially, depress pump until primed.
- Spray one dose directly into mouth.
- Adults 12 and up: 3 sprays 3 times per day
- Children 2-12: 2 sprays 3 times per day
- Use additionally as needed, up to 6 times per day.

OTHER SAFETY INFORMATION

Tamper resistant for your protection. Use only if safety seal is intact. This product has not been clinically tested.

PURPOSE

Uses for temporary relief of:

- muscle and joint soreness
- aches
- morning stiffness
- bruises and tightness after sports participation, exercise, or exertion